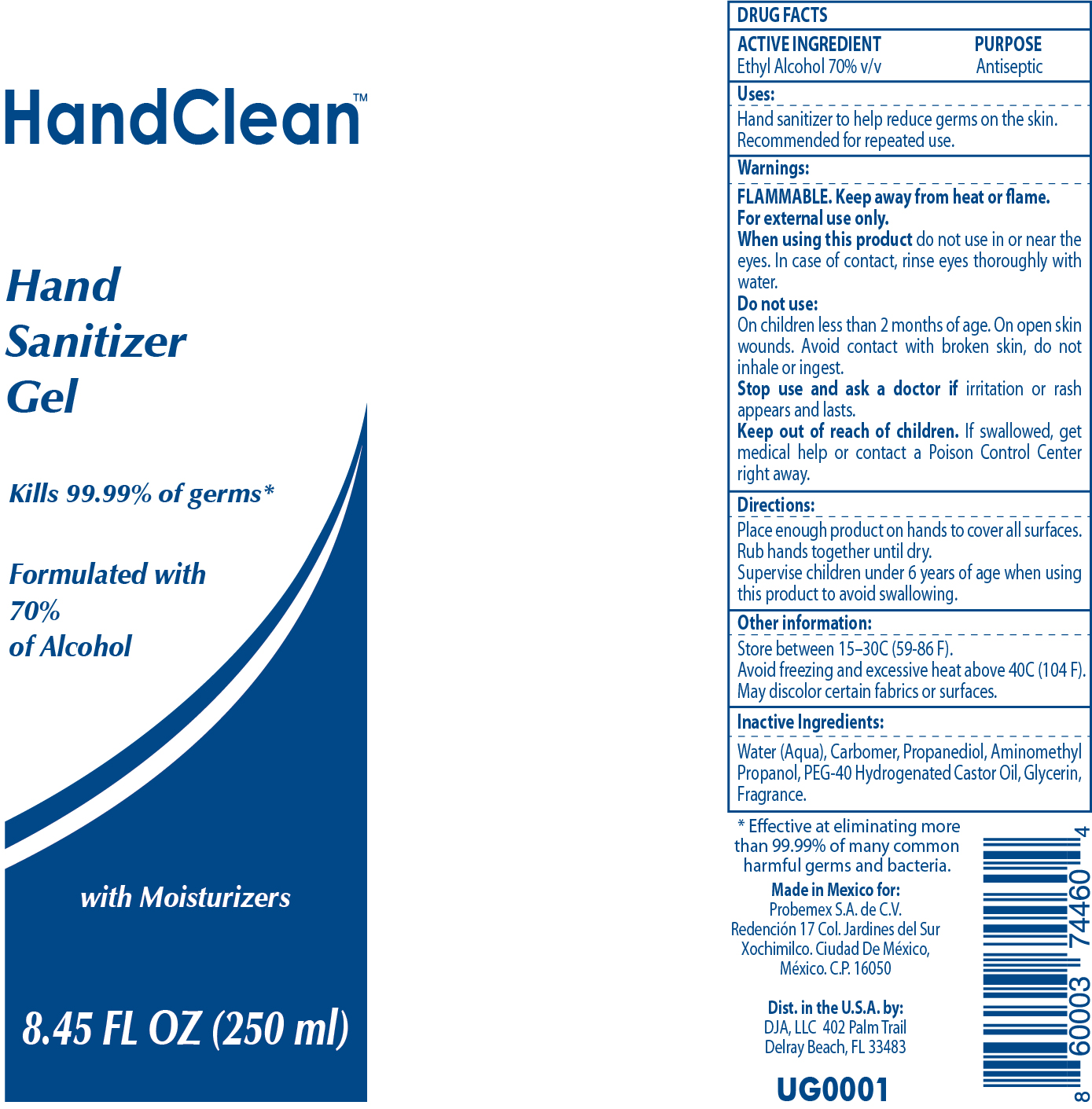 DRUG LABEL: HAND SANITIZER HAND CLEAN
NDC: 42955-010 | Form: GEL
Manufacturer: PROBEMEX S.A. DE CV
Category: otc | Type: HUMAN OTC DRUG LABEL
Date: 20200812

ACTIVE INGREDIENTS: ALCOHOL 70 mL/100 mL
INACTIVE INGREDIENTS: CARBOXYPOLYMETHYLENE 0.33 mL/100 mL; HYDROGENATED CASTOR OIL 0.14 mL/100 mL; GLYCERIN 0.001 mL/100 mL; PROPANEDIOL 0.51 mL/100 mL; WATER 27.9 mL/100 mL; AMINOMETHYL PROPANEDIOL 0.22 mL/100 mL

HAND SANITIZER

This is a hand sanitizer manufactured according to the Temporary Policy for Preparation of Certain Alcohol-Based Hand Sanitizer Products During the Public Health Emergency (CoViD-19); Guidance for Industry.

The hand sanitizer is manufactured using only the following United States Pharmacopoeia (USP) grade ingredients in the preparation of the product (percentage in final product formulation) consistent with World Health Organization (WHO) recommendations:

1. Alcohol (ethanol) (USP or Food Chemical Codex (FCC) grade) (70%, volume/volume (v/v)) in an aqueous solution denatured according to Alcohol and Tobacco Tax and Trade Bureau regulations in 27 CFR part 20.

Active Ingredient(s)

Ethyl Alcohol 70%

Purpose

Antiseptic,

Use

Hand Sanitizer to help reduce bacteria that potentially can cause disease. For use when soap and water are not available.

Warnings

For external use only. Flammable. Keep away from heat or flame

Do not use

- in children less than 2 months of age
- on open skin wounds

When using this product keep out of eyes, ears, and mouth. In case of contact with eyes, rinse eyes thoroughly with water.
Stop use and ask a doctor if irritation or rash occurs. These may be signs of a serious condition.
Keep out of reach of children. If swallowed, get medical help or contact a Poison Control Center right away.

Stop use and ask a doctor if irritation or rash occurs. These may be signs of a serious condition.

Keep out of reach of children. If swallowed, get medical help or contact a Poison Control Center right away.

Directions

- Place enough product on hands to cover all surfaces. Rub hands together until dry.
- Supervise children under 6 years of age when using this product to avoid swallowing.

Other information

- Store between 15-30C (59-86F)
- Avoid freezing and excessive heat above 40C (104F)

Inactive ingredients

Water, carbomer, propanediol aminomethyl propanol hydrogenated castor oil glycerin

Package Label - Principal Display Panel

42955-010-01

42955-010-02

42955-010-03